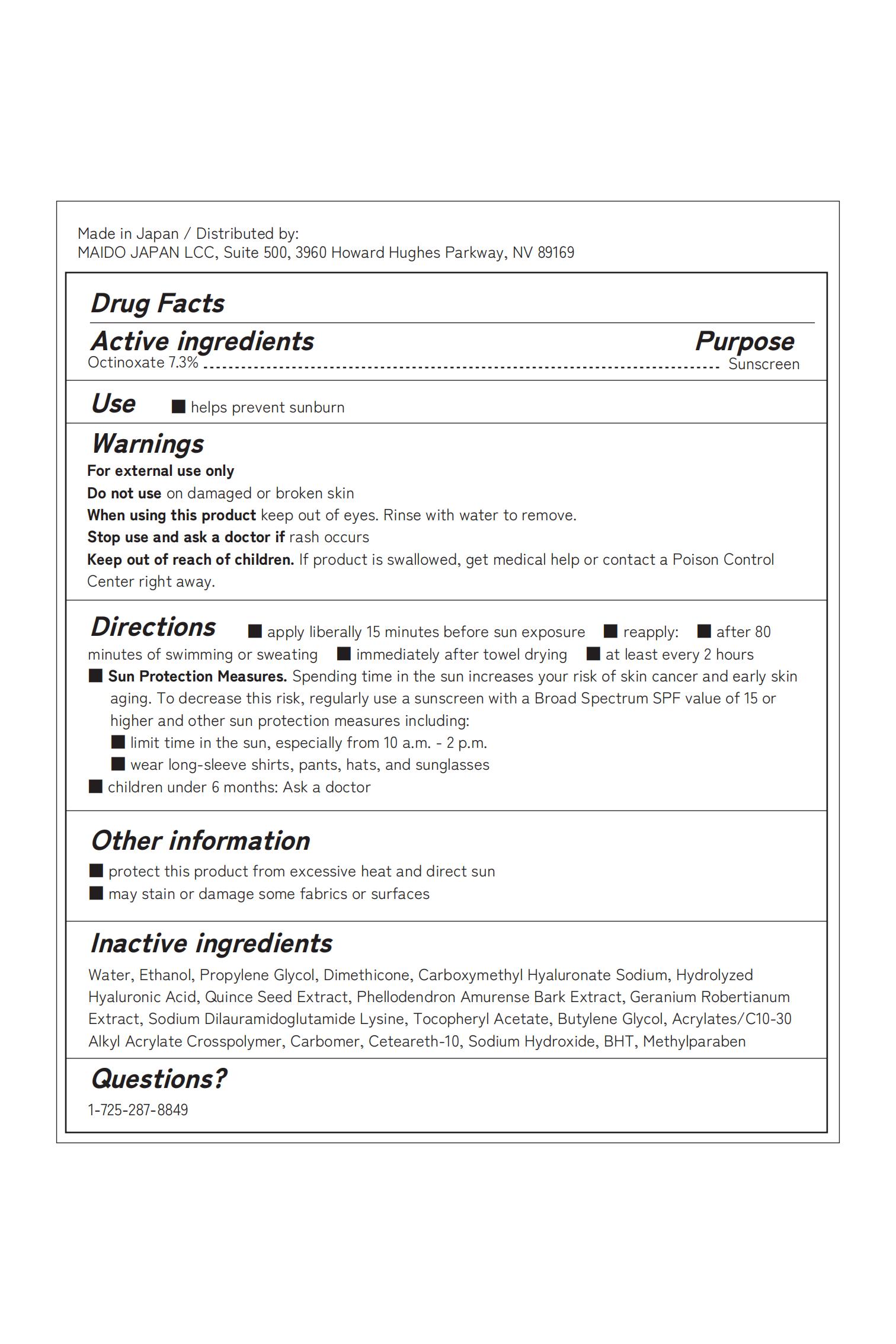 DRUG LABEL: Sunscreen
NDC: 87243-123 | Form: CREAM
Manufacturer: MAIDORA CO.,LTD
Category: homeopathic | Type: HUMAN OTC DRUG LABEL
Date: 20251120

ACTIVE INGREDIENTS: OCTINOXATE 1 g/1 1
INACTIVE INGREDIENTS: BENZALDEHYDE PROPYLENE GLYCOL ACETAL; SODIUM DILAURAMIDOGLUTAMIDE LYSINE; CETEARETH-10; BHT; METHYLPARABEN; ACRYLATES/C10-30 ALKYL ACRYLATE CROSSPOLYMER (60000 MPA.S); CARBOMER; WATER; (4-METHOXYPHENYL)DIPHENYLMETHANOL; DIMETHICONE 20; SODIUM HYDROXIDE

ACTIVE INGREDIENT

Octinoxate

PURPOSE

helps prevent sunburn

keep out of reach of children

INDICATIONS AND USAGE

helps prevent sunburn
apply liberally 15 minutes before sun exposure
after 80 minutes of swimming or sweating

immediately after towel drying

WARNINGS

keep out of eyes. Rinse with water to remove

DOSAGE AND ADMINISTRATION

helps prevent sunburn

INACTIVE INGREDIENT

Water,Propylene Glycol,Dimethicone,Sodium Dilauramidoglutamide Lysine,Tocopheryl Acetate,Butylene Glycol,Acrylates/C10-30 Alkyl Acrylate Crosspolymer,Carbomer,Ceteareth-10,Sodium Hydroxide,BHT,Methylparaben